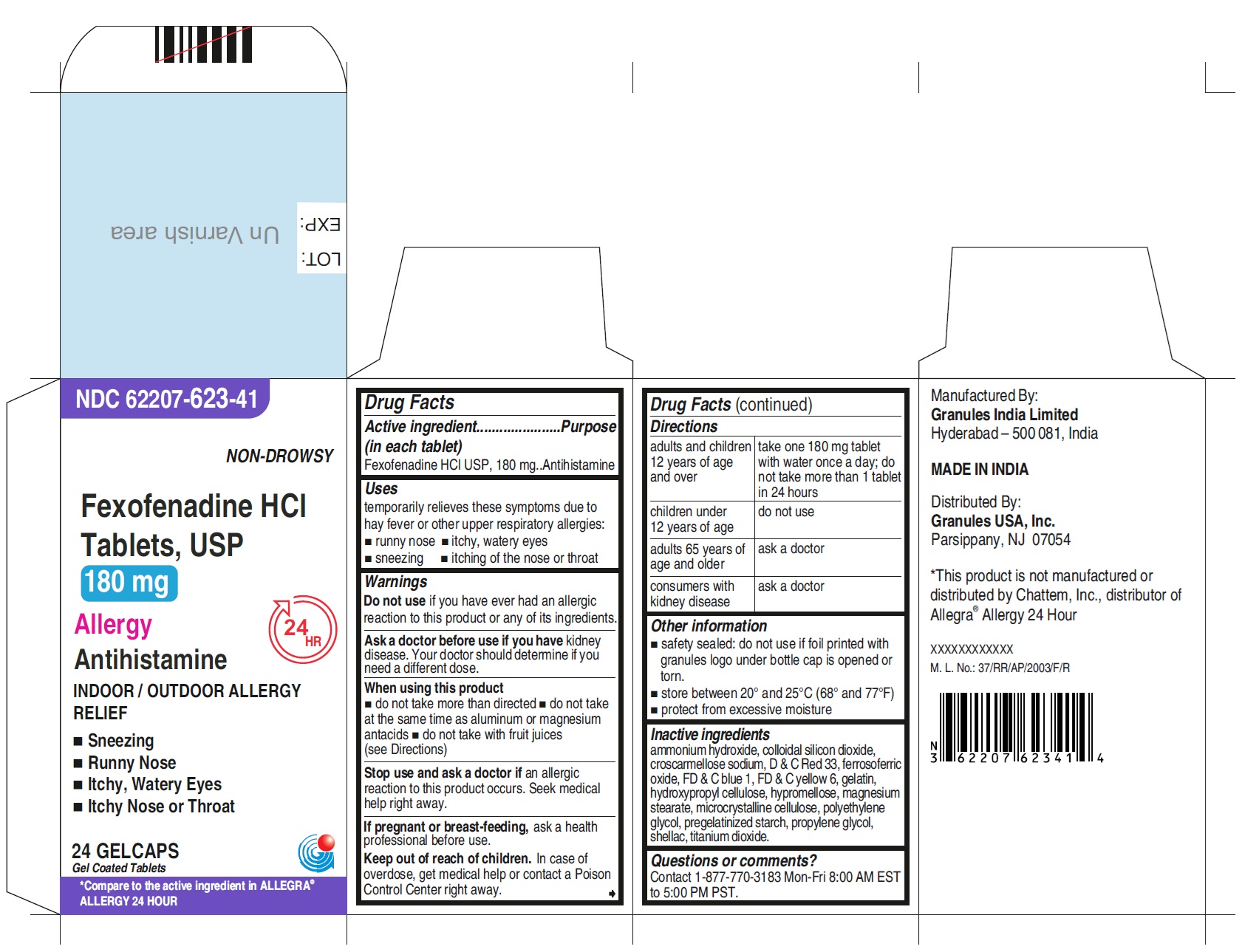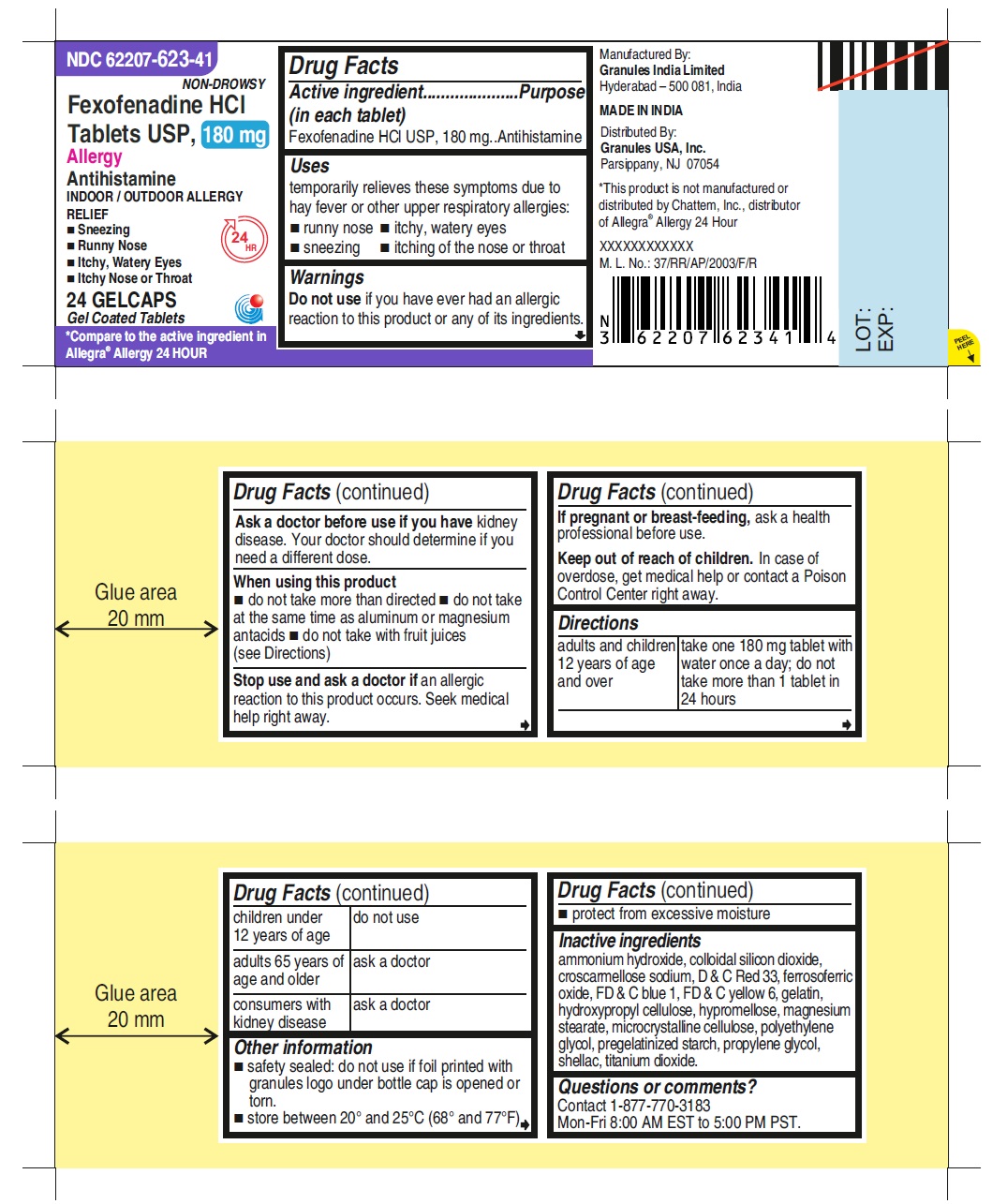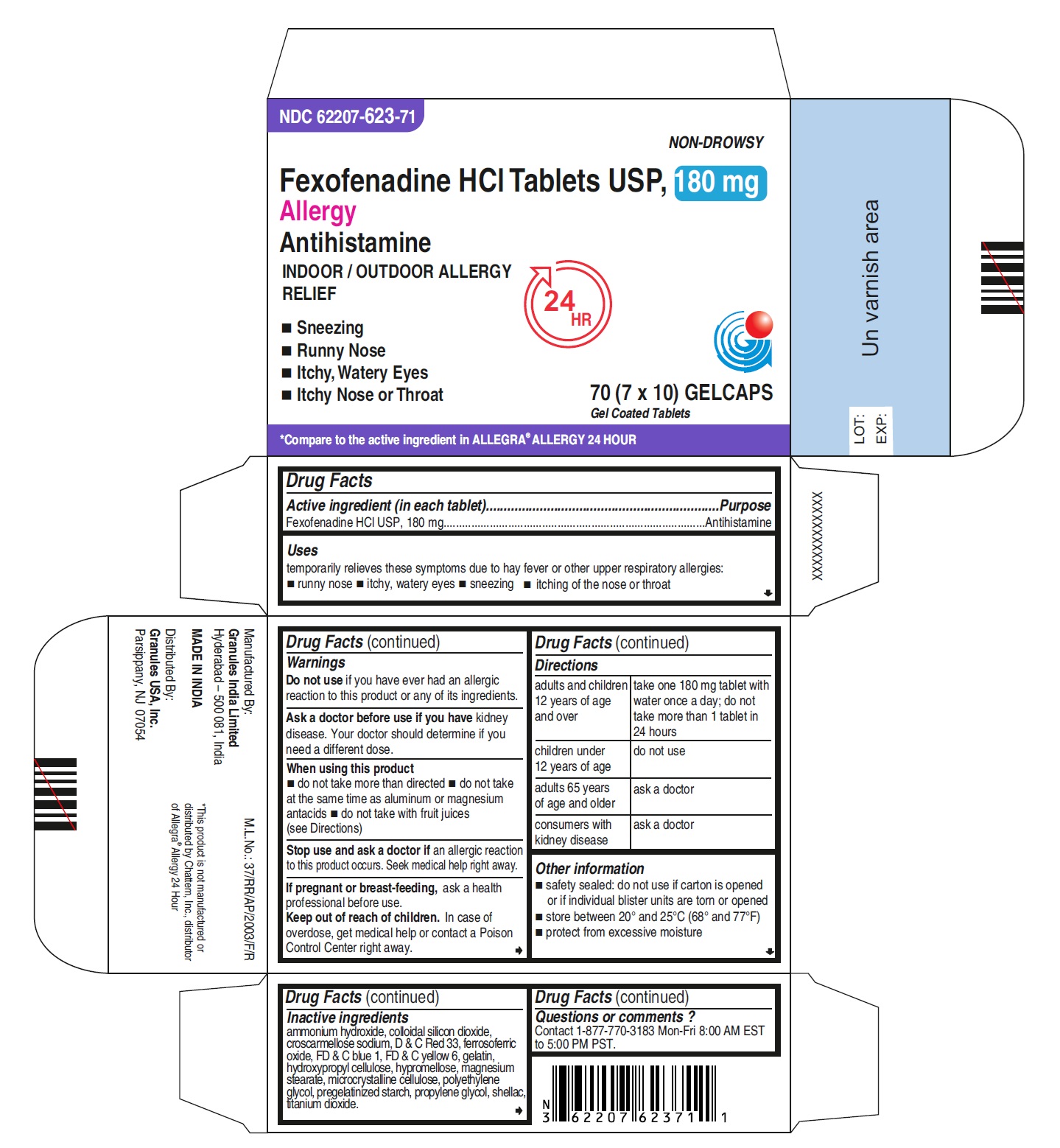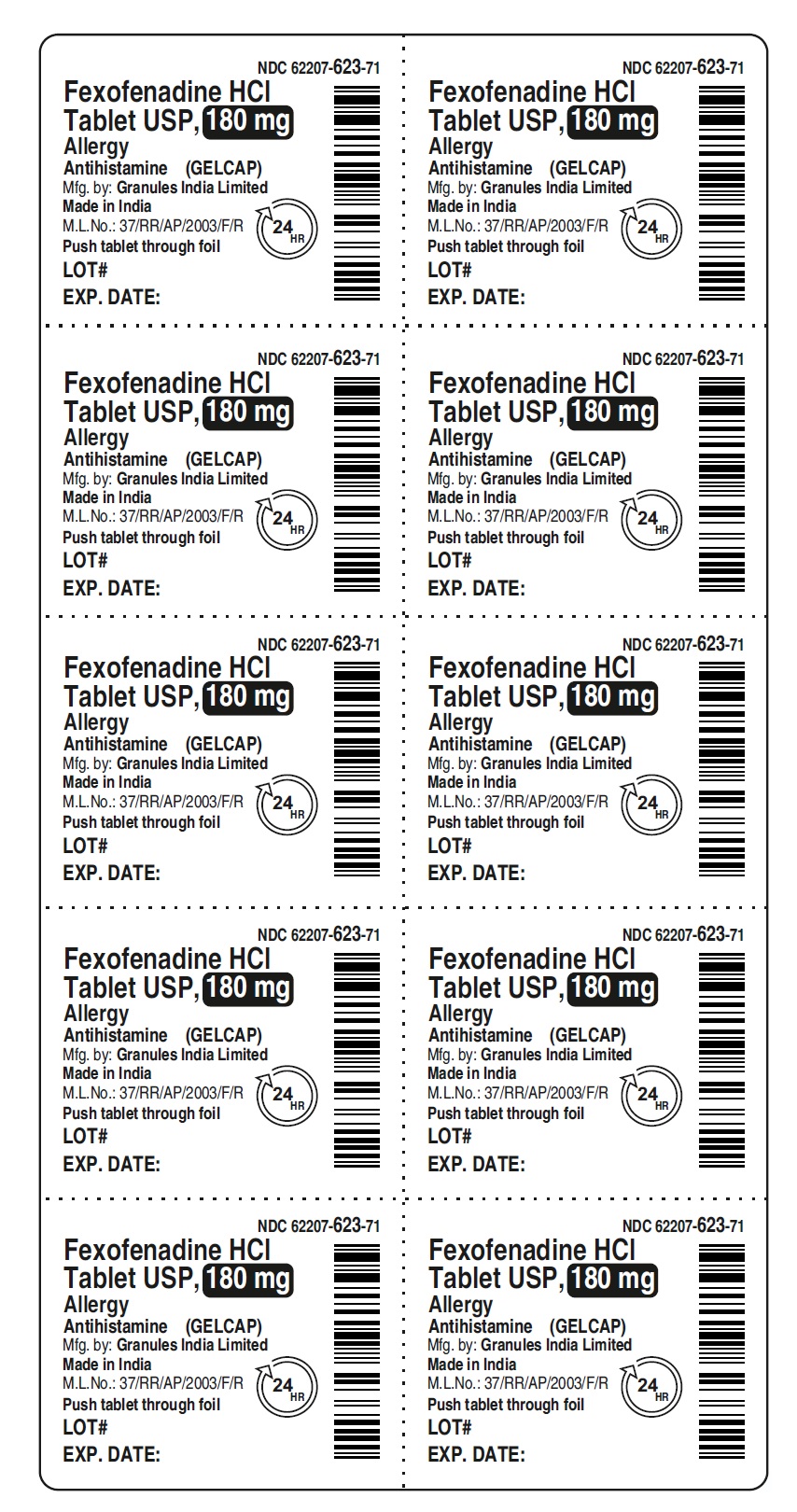 DRUG LABEL: Fexofenadine Hydrochloride
NDC: 62207-623 | Form: TABLET
Manufacturer: Granules India Limited
Category: otc | Type: HUMAN OTC DRUG LABEL
Date: 20240808

ACTIVE INGREDIENTS: FEXOFENADINE HYDROCHLORIDE 180 mg/1 1
INACTIVE INGREDIENTS: PROPYLENE GLYCOL; GELATIN; HYDROXYPROPYL CELLULOSE (90000 WAMW); CROSCARMELLOSE SODIUM; FERROSOFERRIC OXIDE; FD&C BLUE NO. 1; FD&C YELLOW NO. 6; HYPROMELLOSE 2910 (3 MPA.S); MAGNESIUM STEARATE; MICROCRYSTALLINE CELLULOSE; POLYETHYLENE GLYCOL 8000; SILICON DIOXIDE; STARCH, CORN; TITANIUM DIOXIDE; SHELLAC; D&C RED NO. 33; AMMONIA

Fexofenadine HCl Tablets USP, 60 mg and 180 mg

Active ingredient (in each tablet)

Fexofenadine HCl USP, 180 mg

Purpose

Antihistamine

Uses

temporarily relieves these symptoms due to hay fever or other upper respiratory allergies:

- runny nose
- itchy, watery eyes
- sneezing
- itching of the nose or throat

Warnings

Do not use

if you have ever had an allergic reaction to this product or any of its ingredients.

Ask a doctor before use if you have

kidney disease. Your doctor should determine if you need a different dose.

When using this product

- do not take more than directed
- do not take at the same time as aluminum or magnesium antacids
- do not take with fruit juices (see Directions)

Stop use and ask a doctor if

an allergic reaction to this product occurs. Seek medical help right away.

If pregnant or breast-feeding,

ask a health professional before use.

Keep out of reach of children.

In case of overdose, get medical help or contact a Poison Control Center right away.

Directions

adults and children 12 years of age and over | take one 180 mg tablet with water once a day; do not take more than 1 tablet in 24 hours
children under 12 years of age | do not use
adults 65 years of age and older | ask a doctor
consumers with kidney disease | ask a doctor

Other information

- safety sealed: do not use if carton is opened or if individual blister units are torn or opened
- store between 20º and 25ºC (68º and 77ºF)
- protect from excessive moisture

Inactive ingredients

ammonium hydroxide, colloidal silicon dioxide, croscarmellose sodium, D & C Red 33, ferrosoferric oxide, FD & C blue 1, FD & C yellow 6, gelatin, hydroxypropyl cellulose, hypromellose, magnesium stearate, microcrystalline cellulose, polyethylene glycol, pregelatinized starch, propylene glycol, shellac, titanium dioxide.

Questions or comments?

Contact 1-877-770-3183 Mon-Fri 8:00 AM EST to 5:00 PM PST.
Manufactured By:
Granules India Limited
Hyderabad-500 081, India

MADE IN INDIA
Distributed By:
Granules USA, Inc.
Parsippany, NJ 07054

PRINCIPAL DISPLAY PANEL 180 mg - 24s Container Label

NDC 62207-623-41

NON-DROWSY

Fexofenadine HCl

Tablets USP, 180 mg

Allergy

Antihistamine

INDOOR / OUTDOOR ALLERGY
RELIEF 24HR

- Sneezing
- Runny Nose
- Itchy, Watery Eyes
- Itchy Nose or Throat

24 GELCAPS

Gel Coated Tablets

*Compare to the active ingredient in

Allegra® Allergy 24 HOUR

PRINCIPAL DISPLAY PANEL 180 mg -24s Container Carton

NDC 62207-623-41
NON-DROWSY

Fexofenadine HCl
Tablets, USP

180 mg

Allergy

Antihistamine
INDOOR / OUTDOOR ALLERGY
RELIEF 24 HR

- Sneezing
- Runny Nose
- Itchy, Watery Eyes
- Itchy Nose or Throat

24 GELCAPS
Gel Coated Tablets

*Compare to the active ingredient in Allegra®

Allergy 24 HOUR

PRINCIPAL DISPLAY PANEL 180 mg - Blister Carton

NDC 62207-623-71
NON-DROWSY

Fexofenadine HCl Tablets USP, 180 mg

Allergy

Antihistamine

INDOOR / OUTDOOR ALLERGY
RELIEF 24 HR

- Sneezing
- Runny Nose
- Itchy, Watery Eyes
- Itchy Nose or Throat

70 (7x10) GELCAPS

Gel Coated Tablets

*Compare to the active ingredient in ALLEGRA® ALLERGY 24 HOUR

PRINCIPAL DISPLAY PANEL 180 mg - Blister Foil

NDC 62207-623-71
Fexofenadine HCl
Tablet USP, 180 mg
Allergy

Antihistamine (GELCAP)
Mfg. by: Granules India Limited
Made in India

M.L.No.: 37/RR/AP/2003/F/R 24 HR
Push tablet through foil

LOT#
EXP. DATE: